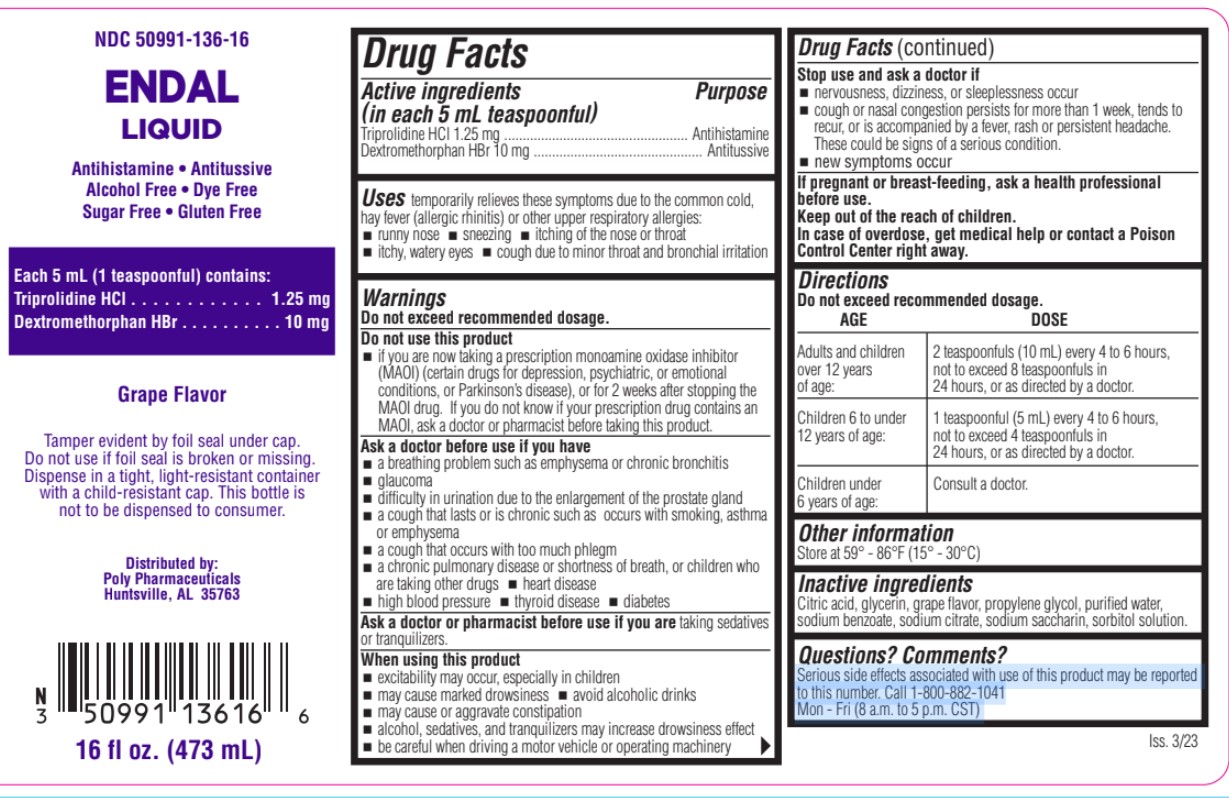 DRUG LABEL: Endal
NDC: 50991-136 | Form: LIQUID
Manufacturer: Poly Pharmaceuticals, Inc.
Category: otc | Type: HUMAN OTC DRUG LABEL
Date: 20251030

ACTIVE INGREDIENTS: TRIPROLIDINE HYDROCHLORIDE 1.25 mg/5 mL; DEXTROMETHORPHAN HYDROBROMIDE 10 mg/5 mL
INACTIVE INGREDIENTS: SORBITOL SOLUTION; CITRIC ACID ACETATE; GLYCERIN; SODIUM CITRATE; WATER; SODIUM BENZOATE; PROPYLENE GLYCOL; SACCHARIN SODIUM

Endal

Active Ingredient

Triprolidine HCl, Dextromethorphan HBr

Purpose

Antihistimine, Antitussive

Uses

Uses temporarily relieves these symptoms due to the common cold, hay fever (allergic rhinitis) or other upper respiratory allergies:

- runny nose
- sneezing
- itching of the nose or throat
- itchy, watery eyes
- cough due to minor throat and bronchial irritation

Warnings

Do not exceed recommended dosage.

Do not use this product

if you are now taking a prescription monoamine oxidase inhibitor (MAOI) (certain drugs for depression, psychiatric, or emotional conditions, or Parkinson’s disease), or for 2 weeks after stopping the MAOI drug. If you do not know if your prescription drug contains an MAOI, ask a doctor or pharmacist before taking this product.

Ask a doctor before use if you have

- a breathing problem such as emphysema or chronic bronchitis
- glaucoma
- difficulty in urination due to the enlargement of the prostate gland
- a cough that lasts or is chronic such as occurs with smoking, asthma or emphysema
- a cough that occurs with too much phlegm
- a chronic pulmonary disease or shortness of breath, or children who are taking other drugs
- heart disease
- high blood pressure
- thyroid disease
- diabetes

Ask a doctor or pharmacist before use

if you are taking sedatives or tranquilizers.

When using this product

- excitability may occur, especially in children
- may cause marked drowsiness
- avoid alcoholic drinks
- may cause or aggravate constipation
- alcohol, sedatives, and tranquilizers may increase drowsiness effect

Stop use and ask a doctor if

- nervousness, dizziness, or sleeplessness occur
- cough or nasal congestion persists for more than 1 week, tends to recur, or is accompanied by a fever, rash or persistent headache.

These could be signs of a serious

- new symptoms occur

If pregnant or breast-feeding,

ask a health professional before use.

Keep out of the reach of children

. In case of overdose, get medical help or contact a Poison Control Center right away.

Directions

AGE | DOSE
Adults and children over 12 years of age | 2 teaspoonfuls (10 mL) every 4 to 6 hours, over 12 years not to exceed 8 teaspoonfuls in of age: 24 hours, or as directed by a doctor.
Children 6 to under 12 years of age | 1 teaspoonful (5 mL) every 4 to 6 hours, 12 years of age: not to exceed 4 teaspoonfuls in 24 hours, or as directed by a doctor.
Children under 6 years of age | Consult a doctor.

Other Information

Store at 59° - 86°F (15° - 30°C)

Inactive Ingredients

Citric acid, glycerin, grape flavor, propylene glycol, purified water, sodium benzoate, sodium citrate, sodium saccharin, sorbitol solution.

Questions? Comments?

Serious side effects associated with use of this product may be reported to this number. Call 1-800-882-1041 Mon - Fri (8 a.m. to 5 p.m. CST)